DRUG LABEL: Canpaco Hand Sanitizer
NDC: 76586-110 | Form: GEL
Manufacturer: HEALKINBIO CO.
Category: otc | Type: HUMAN OTC DRUG LABEL
Date: 20200804

ACTIVE INGREDIENTS: ALCOHOL 62 mL/100 mL
INACTIVE INGREDIENTS: TROLAMINE; .ALPHA.-TOCOPHEROL ACETATE; CARBOMER 940; GLYCERIN; CASTOR OIL; GREEN TEA LEAF; WATER

Active Ingredient(s)

alcohol

Purpose

• Antiseptic (skin) cleanser • Medicated (skin) cleanser • Antibacterial (skin)
cleanser • active in destroying (harmful) bacteria to provide antiseptic
cleansing • For personal hand hygiene to help prevent the spread of bacteria

Use

 Hand sanitizing to help reduce bacteria on the skin

Warnings

For external use only.
Flammable, keep away from fire or flame.
When using this product, avoid contact with the eyes. In case of contact, rinse eyes thoroughly with water.
Stop use and ask a doctor if irritation or redness appears and lasts.

 Keep out of reach of children. If swallowed, get medical help or contact a Poison Control Center immediately.

Directions

for external use only

INACTIVE INGREDIENT

aqua, camellia sinensis leaf extract, carbomer, glycerin, ricinus communis (castor) seed oil, tocopheryl acetate, triethanolamine